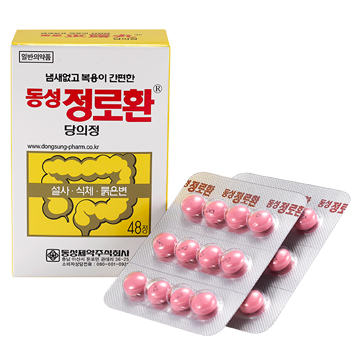 DRUG LABEL: Cheong Ro Hwan Sugar Coated
NDC: 72689-0030 | Form: TABLET, SUGAR COATED
Manufacturer: OASIS TRADING
Category: otc | Type: HUMAN OTC DRUG LABEL
Date: 20181213

ACTIVE INGREDIENTS: WOOD CREOSOTE 22.5 mg/1 1
INACTIVE INGREDIENTS: SUCROSE; SILICON DIOXIDE

ACTIVE INGREDIENT

creosote, phellodendron bark ext. powder, powdered geranium herb

PURPOSE

■ antidiarrhea

Keep out of reach of children

INDICATIONS AND USAGE

■ children under 7 years of age: consult a doctor

■ take 1-2 tablet as symptoms accur, as directed by a doctor

Ask a doctor before use if you have taking a prescription drug. Antacids may interact with certain prescription drugs.

When using this product

■ Do not take more than 4 pills in 24 hours

■ Do not use the maximum dosage for more than 1 weeks

Keep out of the reach of children. This package contains enough drug to seriously harm a child

INACTIVE INGREDIENT

Low Substituted Hydroxymethylcellulose, Sodium Starch Glycolate, Silicon Dioxide, Hypromellose, Sucrose, etc.

DOSAGE AND ADMINISTRATION

For oral use only